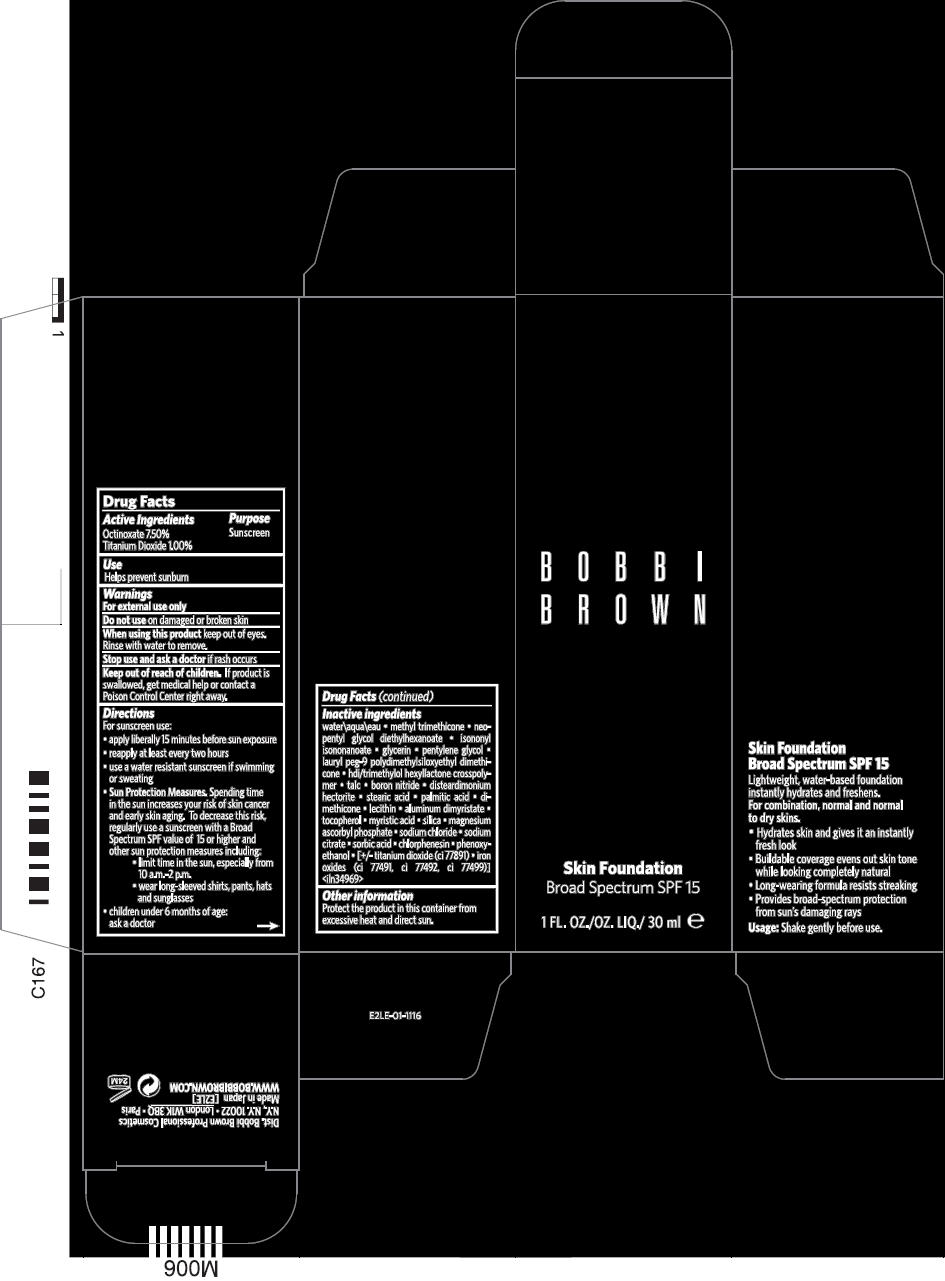 DRUG LABEL: BOBBI BROWN SKIN FOUNDATION
NDC: 64141-013 | Form: LIQUID
Manufacturer: Bobbi Brown Professional Cosmetics Inc.
Category: otc | Type: HUMAN OTC DRUG LABEL
Date: 20241207

ACTIVE INGREDIENTS: OCTINOXATE 75 mg/1 mL; TITANIUM DIOXIDE 10 mg/1 mL
INACTIVE INGREDIENTS: WATER; METHYL TRIMETHICONE; NEOPENTYL GLYCOL DIETHYLHEXANOATE; ISONONYL ISONONANOATE; GLYCERIN; PENTYLENE GLYCOL; TALC; BORON NITRIDE; STEARIC ACID; PALMITIC ACID; DIMETHICONE; ALUMINUM DIMYRISTATE; TOCOPHEROL; MYRISTIC ACID; SILICON DIOXIDE; MAGNESIUM ASCORBYL PHOSPHATE; SODIUM CHLORIDE; SODIUM CITRATE, UNSPECIFIED FORM; SORBIC ACID; CHLORPHENESIN; PHENOXYETHANOL; FERRIC OXIDE RED; FERRIC OXIDE YELLOW; FERROSOFERRIC OXIDE

BOBBI BROWN SKIN FOUNDATION
BROAD SPECTRUM SPF 15

Drug Facts

Active Ingredients

Octinoxate 7.50%
Titanium Dioxide 1.00%

Purpose

Sunscreen

Use

Helps prevent sunburn

Warnings

For external use only

Do not use on damaged or broken skin

When using this product keep out of eyes. Rinse with water to remove.

Stop use and ask a doctor if rash occurs

Keep out of reach of children. If product is swallowed, get medical help or contact a Poison Control Center right away.

Directions

For sunscreen use:

- apply liberally 15 minutes before sun exposure
- reapply at least every two hours
- use a water resistant sunscreen if swimming or sweating
- Sun Protection Measures. Spending time in the sun increases your risk of skin cancer and early skin aging. To decrease this risk, regularly use a sunscreen with a Broad Spectrum SPF value of 15 or higher and other sun protection measures including:
  - limit time in the sun, especially from 10 a.m.-2 p.m.
  - wear long-sleeved shirts, pants, hats and sunglasses
- children under 6 months of age: ask a doctor

Inactive ingredients

water\aqua\eau • methyl trimethicone • neopentyl glycol diethylhexanoate • isononyl isononanoate • glycerin • pentylene glycol • lauryl peg-9 polydimethylsiloxyethyl dimethicone • hdi/trimethylol hexyllactone crosspolymer • talc • boron nitride • disteardimonium hectorite • stearic acid • palmitic acid • dimethicone • lecithin • aluminum dimyristate • tocopherol • myristic acid • silica • magnesium ascorbyl phosphate • sodium chloride • sodium citrate • sorbic acid • chlorphenesin • phenoxyethanol • [+/- titanium dioxide (ci 77891) • iron oxides (ci 77491, ci 77492, ci 77499)] <iln34969>

Other information

Protect the product in this container from excessive heat and direct sun.

Dist. Bobbi Brown Professional Cosmetics
N.Y., N.Y. 10022

PRINCIPAL DISPLAY PANEL - 30 mL Bottle Carton

BOBBI
BROWN

Skin Foundation
Broad Spectrum SPF 15

1 FL. OZ./ 30 ml e